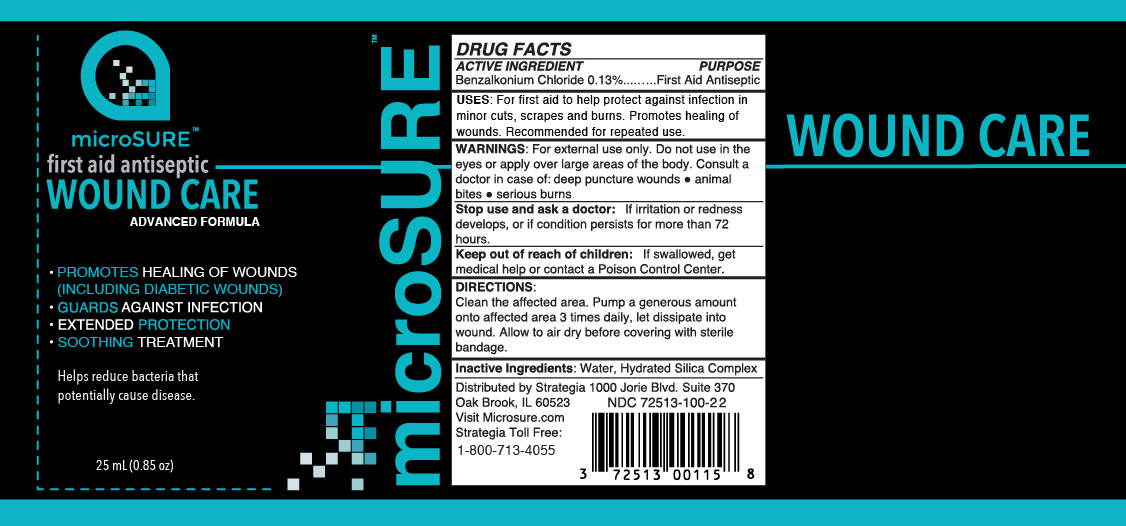 DRUG LABEL: Microsure Wound Care
NDC: 72513-100 | Form: LIQUID
Manufacturer: Strategia Project Management, Inc.
Category: otc | Type: HUMAN OTC DRUG LABEL
Date: 20231220

ACTIVE INGREDIENTS: BENZALKONIUM CHLORIDE 0.13 g/100 mL
INACTIVE INGREDIENTS: HYDRATED SILICA 0.04 g/100 mL; WATER 99.83 g/100 mL

Microsure Wound Care

Active Ingredients

Benzalkonium Chloride.... 0.13%

Purpose

First Aid Antiseptic

Uses

For first aid to help protect against infection in minor cuts, scrapes and burns. Promotes healing of wounds. Recommended for repeated use.

Warnings

For external use only. Do not use in eyes or apply over large areas of the body. Consult a doctor in case of: deep puncture wounds • animal bites • serious burns.

Stop use and ask a doctor if irritation or redness develops, or if condition persists for more than 72 hours.

Keep out of reach of children. If swallowed, get medical help or contact a Poison Control Center right away.

Directions

Clean the affected area. Pump a generous amount onto affected area 3 times daily, let dissipate into wound. Allow to air dry before covering with sterile bandage.

Directions

For first aid to help protect against infection in minor cuts, scrapes and burns. Promotes healing of wounds. Recommended for repeated use.

Inactive Ingredients

Water, Hydrated Silica Complex

Questions?

Distributed by Strategia

1000 Jorie Blvd. Suite 370

Oak Brook, IL 60523

Visit Microsure.com

Strategia Toll Free:

1-800-713-4055

First Aid Antiseptic

Advanced Formula

• Promotes Healing of Wounds (Including Diabetic Wounds)

• Guards Against Infection

• Extended Protection

• Soothing Treatment

Helps reduce bacteria that
potentially cause disease.

25mL (0.85oz)